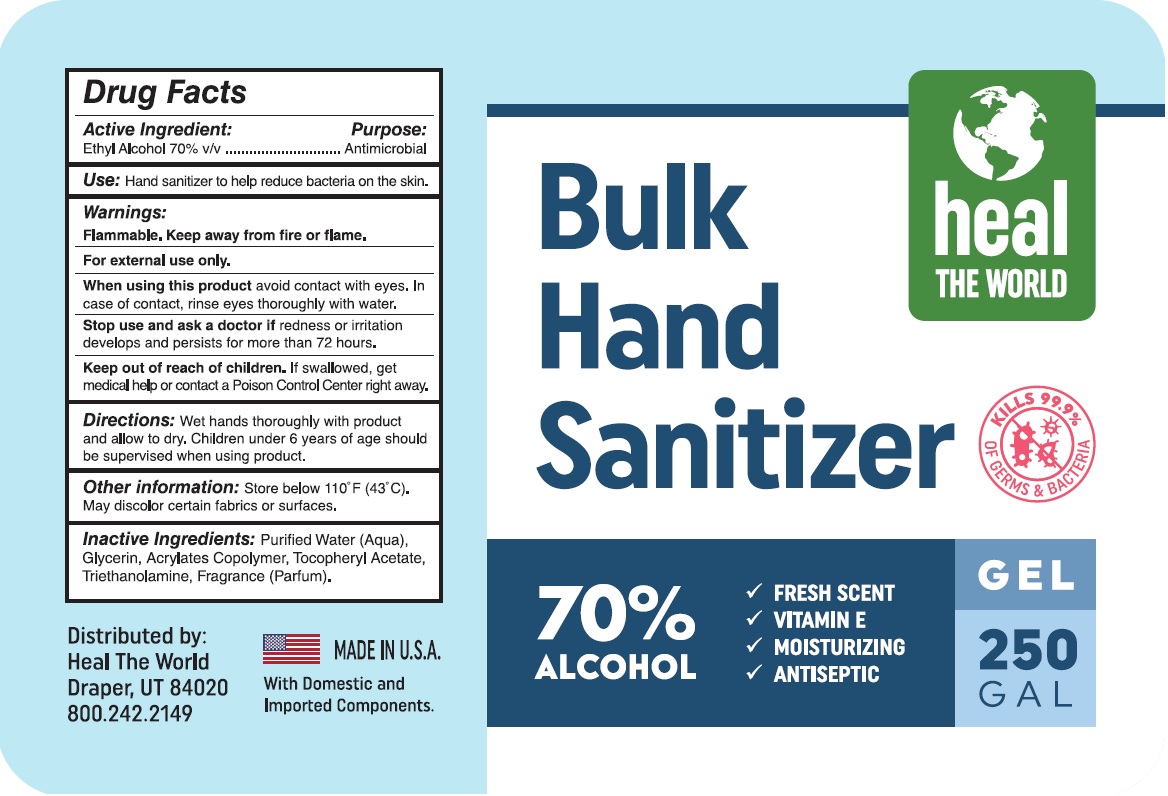 DRUG LABEL: Heal The World Bulk Hand Sanitizer
NDC: 73973-242 | Form: GEL
Manufacturer: HEAL THE WORLD, LLC
Category: otc | Type: HUMAN OTC DRUG LABEL
Date: 20200701

ACTIVE INGREDIENTS: ALCOHOL 70 mL/100 mL
INACTIVE INGREDIENTS: WATER; GLYCERIN; METHACRYLIC ACID - ETHYL ACRYLATE COPOLYMER (4500 MPA.S); .ALPHA.-TOCOPHEROL ACETATE; TROLAMINE

heal THE WORLD Bulk Hand Sanitizer

Active Ingredient:

Ethyl Alcohol 70% v/v

Purpose:

Antimicrobial

INDICATIONS AND USAGE

Use: Hand sanitizer to help reduce bacteria on the skin.

Warnings:

Flammable. Keep away from fire or flame.

For external use only.

When using this product avoid contact with eyes. In case of contact, rinse eyes thoroughly with water.

Stop use and ask a doctor if redness or irritation develops and persists for more than 72 hours.

Keep out of reach of children. If swallowed, get medical help or contact a Poison Control Center right away.

DOSAGE AND ADMINISTRATION

Directions: Wet hands thoroughly with product and allow to dry. Children under 6 years of age should be supervised when using product.

Other information: Store below 110ºF (43ºC). May discolor certain fabrics or surfaces.

INACTIVE INGREDIENT

Inactive Ingredients: Purified Water (Aqua), Glycerin, Acrylates Copolymer, Tocopheryl Acetate, Triethanolamine, Fragrance (Parfum).

KILLS 99.9% OF GERMS & BACTERIA

- FRESH SCENT
- VITAMIN E
- MOISTURIZING
- ANTISEPTIC

Distributed by:

Heal The World

Draper, UT 84020

800.242.2149

MADE IN U.S.A.

With Domestic and Imported Components.